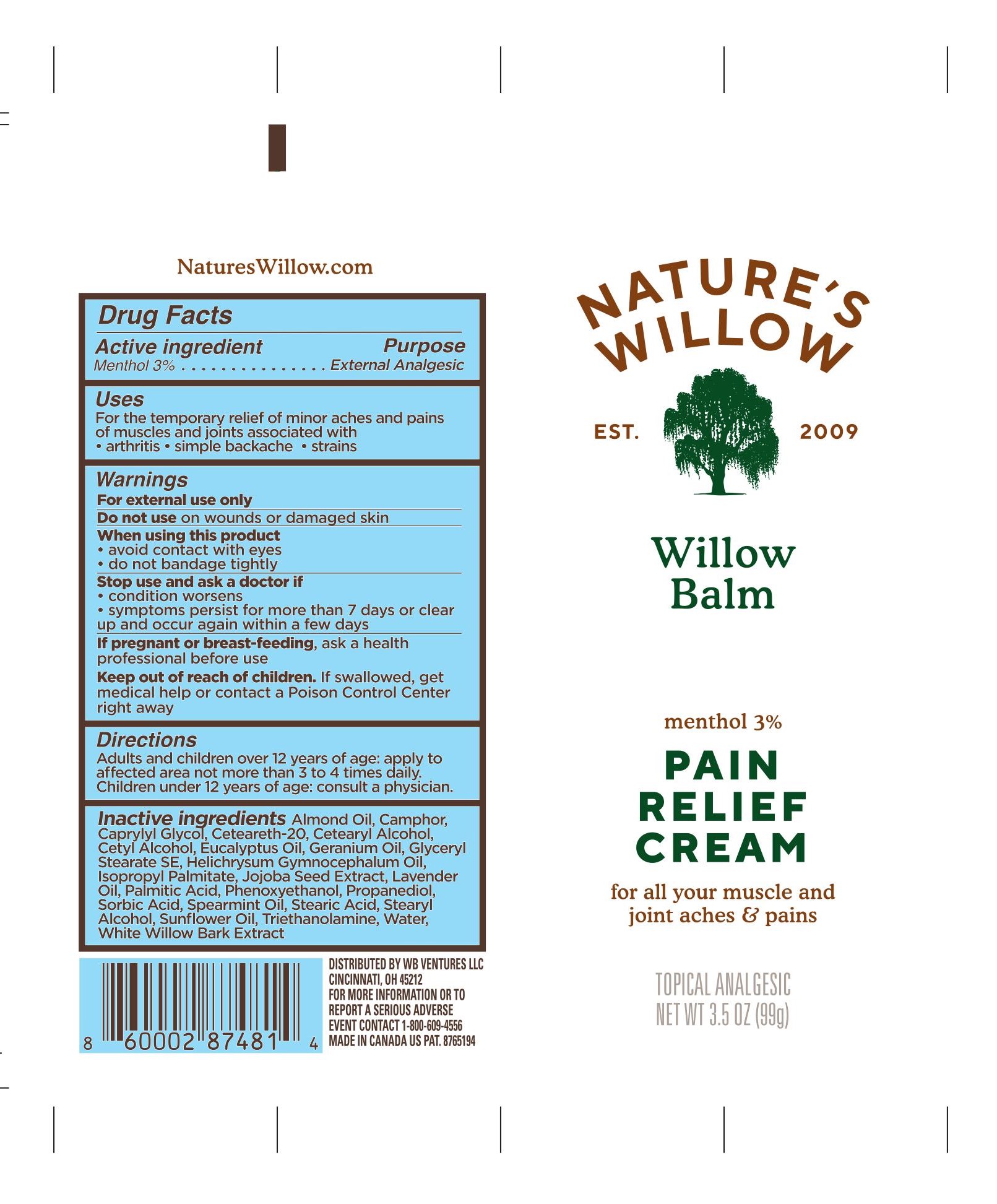 DRUG LABEL: Natures Willow Balm
NDC: 73498-021 | Form: CREAM
Manufacturer: WB VENTURES LLC
Category: otc | Type: HUMAN OTC DRUG LABEL
Date: 20231219

ACTIVE INGREDIENTS: MENTHOL 30 mg/1 g
INACTIVE INGREDIENTS: CAMPHOR (SYNTHETIC); CAPRYLYL GLYCOL; CETOSTEARYL ALCOHOL; POLYOXYL 20 CETOSTEARYL ETHER; ALMOND OIL; STEARYL ALCOHOL; SPEARMINT OIL; SORBIC ACID; PHENOXYETHANOL; PALMITIC ACID; EUCALYPTUS OIL; SUNFLOWER OIL; CETYL ALCOHOL; SALIX ALBA BARK; WATER; TROLAMINE; HELICHRYSUM GYMNOCEPHALUM WHOLE; STEARIC ACID; PROPANEDIOL; LAVENDER OIL; PELARGONIUM GRAVEOLENS FLOWER OIL; SIMMONDSIA CHINENSIS SEED; ISOPROPYL PALMITATE; GLYCERYL STEARATE SE

Nature's Willow Balm

SPL Unclassified Section

Drug Facts

Active ingredient

Menthol 3%

Purpose

External Analgesic

Uses

For the temporary relief of minor aches and pains of muscles and joints associated with

- arthritis

- simple backache

- strains

Warnings

For external use only

Do not use on wounds or damaged skin

When using this product

- avoid contact with eyes

- do not bandage tightly

Stop use and ask a doctor if

- condition worsens

- symptoms persist for more than 7 days or clear up and occur again within a few days

If pregnant or breast-feeding, ask a health professional before use

Keep out of reach of children. If swallowed, get medical help or contact a Poison Control Center right away

Directions

Adults and children over 12 years of age: apply to affected area not more than 3 to 4 times daily.

Children under 12 years of age: consult a physician.

Inactive ingredients

Almond Oil, Camphor, Caprylyl Glycol, Ceteareth-20, Cetearyl Alcohol, Cetyl Alcohol, Eucalyptus Oil, Geranium Oil, Glyceryl Stearate SE, Helichrysum Gymnocephalum Oil, Isopropyl Palmitate, Jojoba Seed Extract, Lavender Oil, Palmitic Acid, Phenoxyethanol, Propanediol, Sorbic Acid, Spearmint Oil, Stearic Acid, Stearyl Alcohol, Sunflower Oil, Triethanolamine, Water, White Willow Bark Extract

SPL Unclassified Section

Distributed by WB Ventures LLC, Cincinnati, OH 45212

For more information or to report a serious adverse event contact 1-888-609-4556